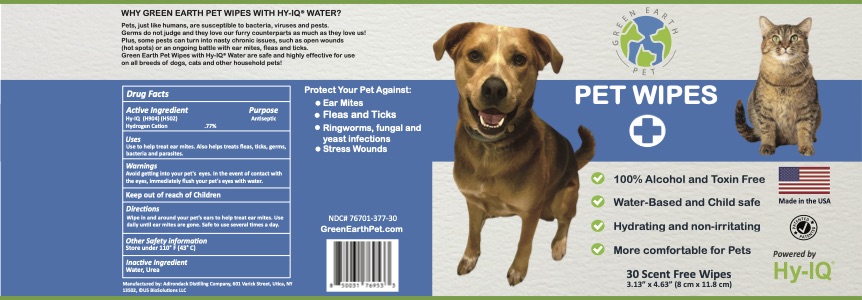 DRUG LABEL: Green Earth Pet Wipes
NDC: 76701-375 | Form: CLOTH
Manufacturer: HAND SANITIZER LLC
Category: animal | Type: OTC ANIMAL DRUG LABEL
Date: 20210821

ACTIVE INGREDIENTS: HYDROGEN CATION 10 mg/1 mL
INACTIVE INGREDIENTS: WATER 940 mg/1 mL; UREA 50 mg/1 mL

Green Earth Pet Wipes

Active Ingredient

Hy-IQ (H904) (H502)
Hydrogen Cation .77%

Purpose

Antiseptic

Uses

Use to help treat ear mites. Also helps treats fleas, ticks, germs, bacteria and parasites.

Warnings

Avoid getting into your pet's eyes. In the event of contact with the eyes, immediately flush your pet's eyes with water.

Keep Out of Reach of Children

Directions

Wipe in and around your pet's ears to help treat ear mites. Use daily until ear mites are gone. Safe to use several times a day.

Other Safety Information

Store under 110º F (43º C)

Inactive Ingredients

Water, Urea

Green Earth Pet Wipes